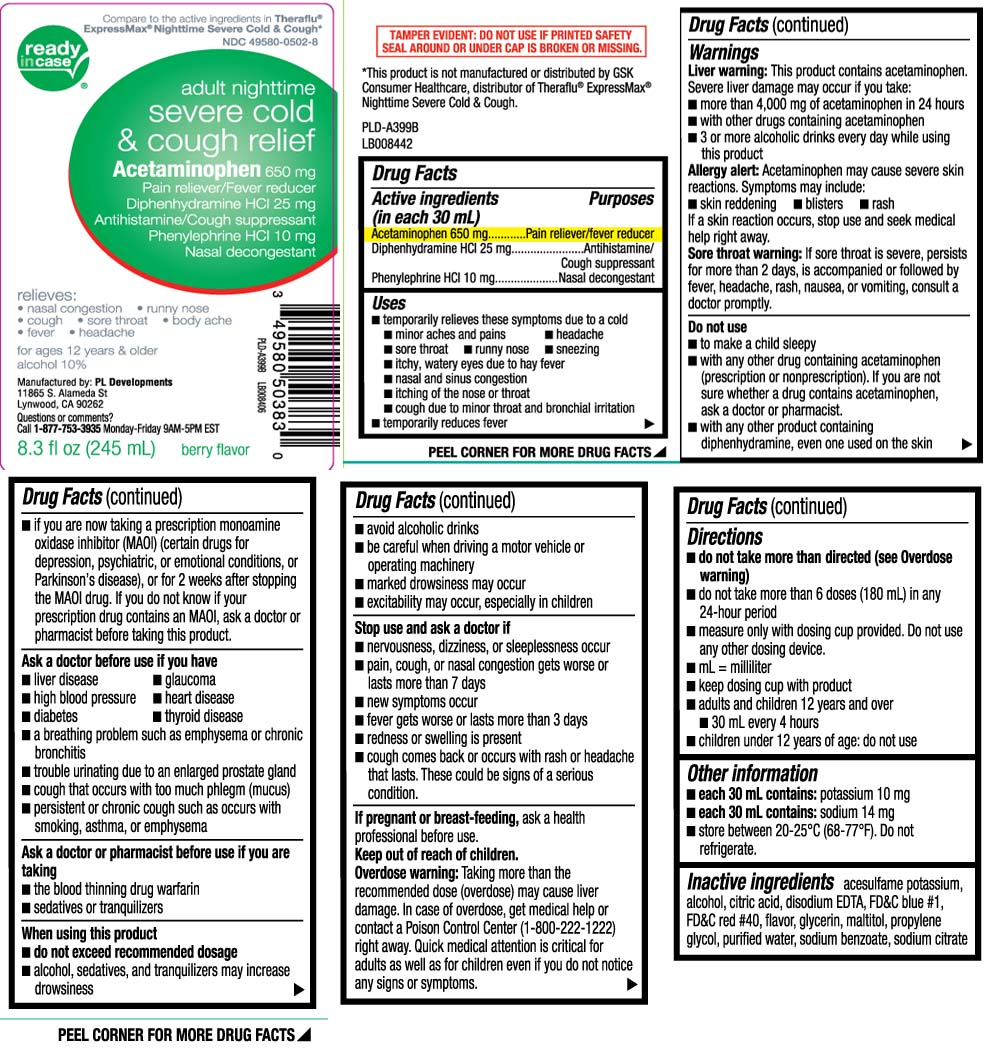 DRUG LABEL: Nighttime Severe Cold and Cough
NDC: 49580-0502 | Form: LIQUID
Manufacturer: P & L Development, LLC
Category: otc | Type: HUMAN OTC DRUG LABEL
Date: 20240415

ACTIVE INGREDIENTS: ACETAMINOPHEN 650 mg/30 mL; DIPHENHYDRAMINE HYDROCHLORIDE 25 mg/30 mL; PHENYLEPHRINE HYDROCHLORIDE 10 mg/30 mL
INACTIVE INGREDIENTS: ACESULFAME POTASSIUM; ALCOHOL; ANHYDROUS CITRIC ACID; EDETATE DISODIUM; FD&C BLUE NO. 1; FD&C RED NO. 40; GLYCERIN; MALTITOL; PROPYLENE GLYCOL; WATER; SODIUM BENZOATE; TRISODIUM CITRATE DIHYDRATE

Drug Facts

Active ingredients (in each 30 mL)

Acetaminophen 650 mg

Diphenhydramine HCl 25 mg

Phenylephrine HCl 10 mg

Purposes

Pain reliever/fever reducer

Antihistamine/Cough suppressant

Nasal decongestant

Uses

- temporarily relieves there symptoms due to a cold
  - minor aches and pains
  - headache
  - sore throat
  - runny nose
  - sneezing
  - itchy, watery eyes due to hay fever
  - nasal and sinus congestion
  - itching of the nose or throat
  - cough due to minor throat and bronchial irritation
- temporarily reduces fever

Warnings

Liver warning: This product contains acetaminophen. Severe liver damage may occur if you take:

- more than 4,000 mg of acetaminophen in 24 hours
- with other drugs containing acetaminophen
- 3 or more alcoholic drinks every day while using this product

Allergy alert: Acetaminophen may cause severe skin reactions. Symptoms may include:

- skin reddening
- blisters
- rash

Sore throat warning: If sore throat is severe, persists for more than 2 days, is accompanied or followed by fever, headache, rash, nausea, or vomiting, consult a doctor promptly.

Do not use

- to make a child sleepy
- if you are now taking a prescription monoamine oxidase inhibitor (MAOI) (certain drugs for depression, psychiatric or emotional conditions, or Parkinson’s disease), or for 2 weeks after stopping the MAOI drug. If you do not know if your prescription drug contains an MAOI, ask a doctor or pharmacist before taking this product.
- with any other product containing diphenhydramine, even one used on skin
- with any other drug containing acetaminophen (prescription or non-prescription). If you are not sure whether a drug contains acetaminophen, ask a doctor or pharmacist.

Ask a doctor before use if you have

- liver disease
- glaucoma
- heart disease
- thyroid disease
- high blood pressure
- diabetes
- cough that occurs with too much phlegm (mucus)
- trouble urinating due to an enlarged prostate gland
- a breathing problem such as emphysema or chronic bronchitis
- persistent or chronic cough such as occurs with smoking, asthma, or emphysema

Ask a doctor or pharmacist before use if you are taking

- the blood thinning drug warfarin
- sedatives or tranquilizers

When using this product

- do not exceed recommended dosage
- alcohol, sedatives, and tranquilizers may increase drowsiness
- avoid alcohol drinks
- be careful when driving a motor vehicle or operating machinery
- marked drowsiness may occur
- excitability may occur, especially in children

Stop use and ask a doctor if

- nervousness, dizziness, or sleeplessness occur
- pain, cough or nasal congestion gets worse or lasts more than 7 days
- new symptoms occur
- fever gets worse or lasts more than 3 days
- redness or swelling is present
- cough comes back or occurs with rash or headache that lasts

These could be signs of a serious condition.

If pregnant or breast-feeding,

ask a health professional before use.

Keep out of reach of children.

Overdose warning: Taking more than the recommended dose (overdose) may cause liver damage. In case of overdose, get medical help or contact a Poison Control Center (1-800-222-1222) right away. Quick medical attention is critical for adults as well as for children even if you do not notice any signs or symptoms.

Directions

- do not take more than directed (see overdose warning)
- do not take more than 6 doses (180 mL) in any 24-hour period
- measure only with dosing cup provided. Do not use any other dosing device
- mL=milliliter
- keep dosing cup with product
- adults and children 12 years and over
  - 30 mL every 4 hours
- children under 12 years of age; do not use

Other information

- each 30 mL contains: potassium 10 mg
- each 30 mL contains: sodium 14 mg
- store between 20-25ºC (68-77ºF). Do not refrigerate.

Inactive ingredients

acesulfame potassium, alcohol, citric acid, edetate disodium, FD&C blue #1, FD&C red #40, flavors, glycerin, maltitol, propylene glycol, purified water, sodium benzoate, sodium citrate

Principal Display Panel

Compare to the active ingredients in Theraflu® ExpressMax® Nighttime Severe Cold & Cough *

adult nighttime Severe Cold & Cough relief

Acetaminophen 650 mg

Pain reliever/Fever reducer

Diphenhydramine HCl 25 mg

Antihistamine/Cough Suppressant

Phenylephrine HCl 10 mg

Nasal decongestant

relieves:

- Nasal Congestion
- runny nose
- cough
- sore throat
- body ache
- Fever
- headache

for ages 12 years & older

alcohol 10%

berry flavor

FL OZ (mL)

TAMPER EVIDENT: DO NOT USE IF PRINTED SAFETY SEAL AROUND OR UNDER CAP IS BROKEN OR MISSING.

*This product is not manufactured or distributed by GSK Consumer Health, distributor Theraflu® ExpressMax® Nighttime Severe Cold & Cough.

Manufactured by: PL Developments

11865 S. Alameda ST

Lynwood, CA 90262

Questions or comments?

Call 1-877-753-3935 Monday-Friday 9AM-5PM EST

Product Label

READYinCASE Adult Night Time Severe Cold & Cough Relief Berry Flavor